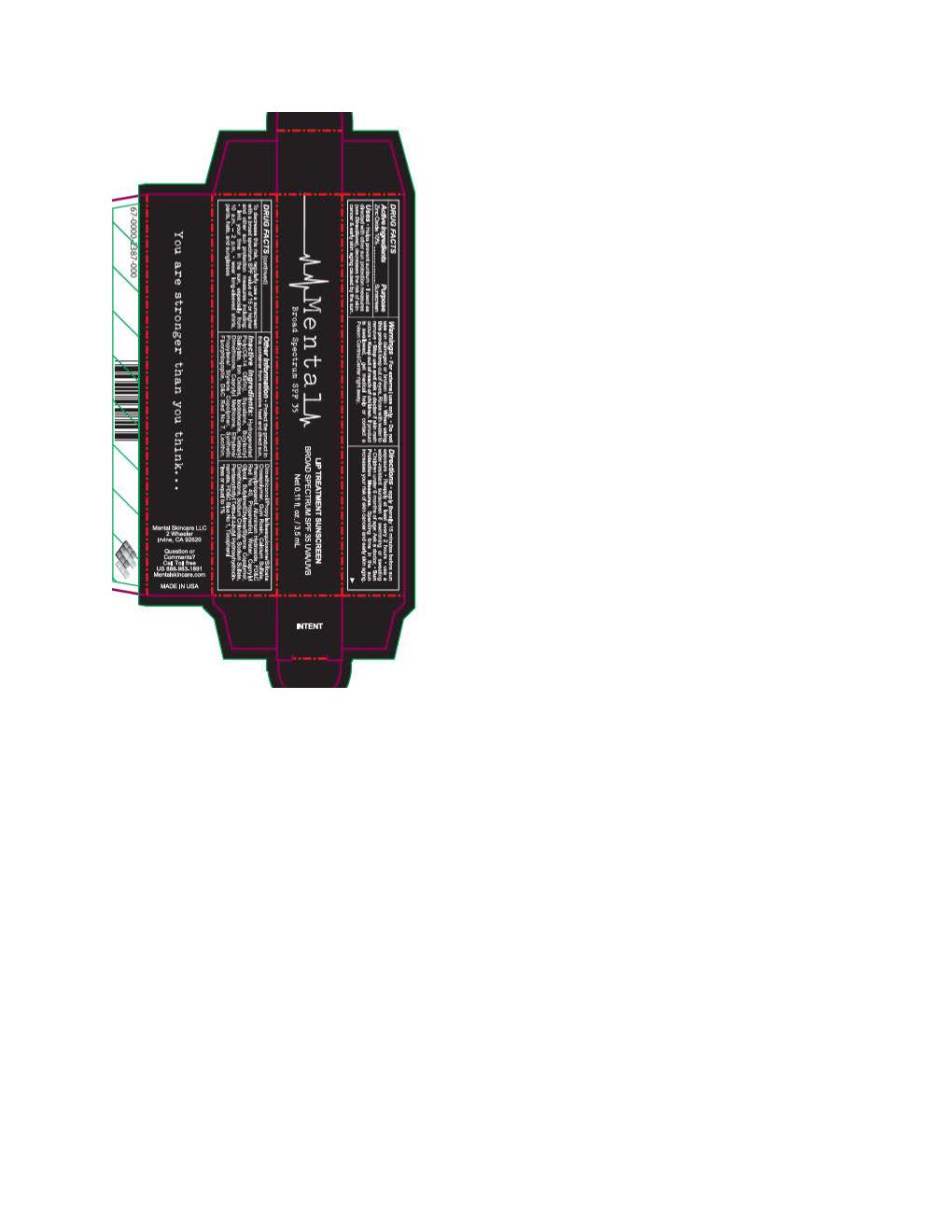 DRUG LABEL: Mental Skin Care Lip Shield
NDC: 82696-0440 | Form: LOTION
Manufacturer: Mental Skin
Category: otc | Type: HUMAN OTC DRUG LABEL
Date: 20251114

ACTIVE INGREDIENTS: ZINC OXIDE 110 mg/1 mL
INACTIVE INGREDIENTS: SQUALANE; FERRIC OXIDE YELLOW; PHENYLPROPANOL; FERROSOFERRIC OXIDE; TOCOPHEROL; PROPANEDIOL; CAPRYLYL GLYCOL; LECITHIN, SOYBEAN; HYDROGENATED POLY(C6-14 OLEFIN; 4 CST); BUTYLOCTYL SALICYLATE; DIMETHICONOL/PROPYLSILSESQUIOXANE/SILICATE CROSSPOLYMER (450000000 MW); DIMETHICONE 1000; ISODODECANE; CAPRYLYL METHICONE; FERRIC OXIDE RED; PENTAERYTHRITYL TETRA-DI-T-BUTYL HYDROXYHYDROCINNAMATE

Mental Skin Care Lip Shield